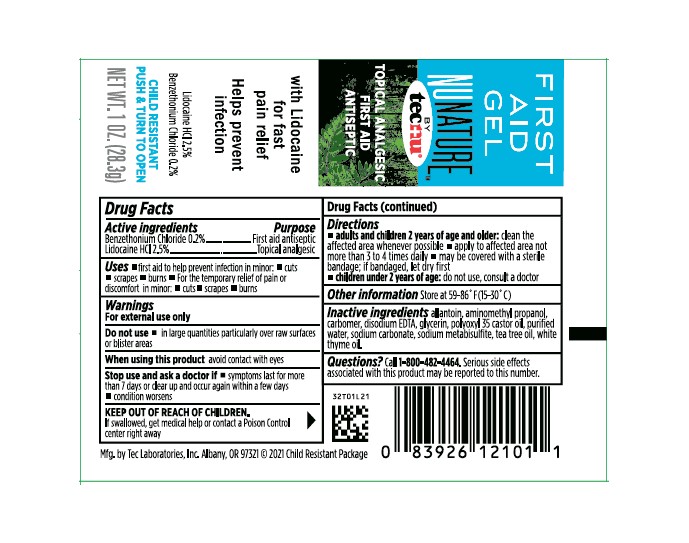 DRUG LABEL: NuNature First Aid Gel
NDC: 51879-211 | Form: GEL
Manufacturer: Tec Laboratories  Inc
Category: otc | Type: HUMAN OTC DRUG LABEL
Date: 20260114

ACTIVE INGREDIENTS: BENZETHONIUM CHLORIDE 2 mg/1 g; LIDOCAINE HYDROCHLORIDE 25 mg/1 g
INACTIVE INGREDIENTS: TEA TREE OIL; CARBOMER HOMOPOLYMER TYPE C (ALLYL PENTAERYTHRITOL CROSSLINKED); GLYCERIN; EDETATE DISODIUM; SODIUM METABISULFITE; THYME OIL; ALLANTOIN; AMINOMETHYLPROPANOL; POLYOXYL 35 CASTOR OIL; SODIUM CARBONATE

NuNature First Aid Gel

ACTIVE INGREDIENT

Benzethonium Chloride 0.2%

Lidocaine Hydrochloride 2.5%

Uses

- First aid to help prevent infection in minor:
- cuts
- scrapes
- burns
- For the temporary relief of pain or discomfort in minor:
- cuts
- scrapes
- burns

Warnings

For external use only

Do not use

- in large quantitiies particularly over raw surfaces or blister areas

When using this product

avoid contact with eyes

Stop use and ask a doctor if

- symptoms last for more than 7 days or clear up and occur again within a few days
- conditions worsens

KEEP OUT OF REACH OF CHILDREN

if swallowed, get medical help or contact Poison Control center right away

Directions

- adults and children 2 years of age and older:clean the affected area whenever possible
- apply to affected area not more than 3 to 4 times daily
- may be covered with a sterile bandange;if bandaged, let dry first
- children under 2 years of age:do not use, consult a doctor

Other information

Store at 59-86ºF(15-30ºC)

INACTIVE INGREDIENT

allantoin, aminomethyl propanol, carbomer, disodium EDTA, glycerin, polyoxyl 35 castor oil, purified water, sodium carbonate, sodium metabisulfite, tea tree oil, white thyme oil.

Questions?

Call 1-800-482-4464.Serious side effects associated with this product may be reported to this number.

PURPOSE

Topical Analgestic and First Aid Antiseptic